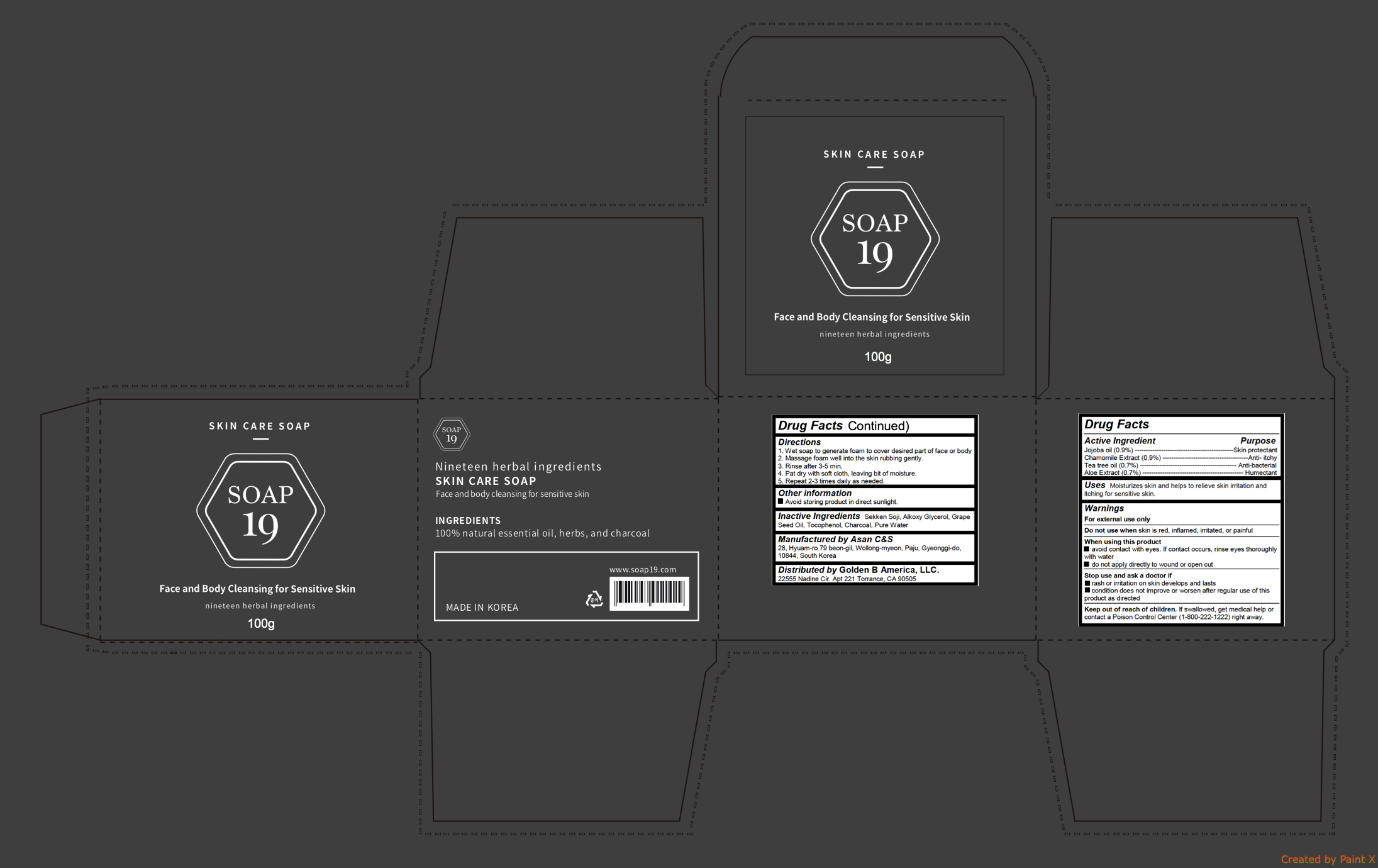 DRUG LABEL: Skin Care
NDC: 72100-103 | Form: SOAP
Manufacturer: Golden B America, LLC.
Category: otc | Type: HUMAN OTC DRUG LABEL
Date: 20180313

ACTIVE INGREDIENTS: JOJOBA OIL 0.9 g/100 g; CHAMOMILE 0.9 g/100 g; ALOE 0.7 g/100 g; TEA TREE OIL 0.7 g/100 g
INACTIVE INGREDIENTS: WATER; GRAPE SEED OIL; TOCOPHEROL; ACTIVATED CHARCOAL

Skin Care Soap

Active ingredients

Jojoba oil (0.9%)

Chamomile Extract (0.9%)

Tea tree oil (0.7%)

Aloe Extract (0.7%)

Purpose

Skin protectant

Anti- itchy

Anti-bacterial

Humectant

Uses

Moisturizes skin and helps to relieve skin irritation and itching for sensitive skin.

Warnings

For external use only

Do not use when skin is red, inflamed, irritated, or painful

When using this product

- avoid contact with eyes. If contact occurs, rinse eyes thoroughly with water
- do not apply directly to wound or open cut

Stop use and ask a doctor if

- rash or irritation on skin develops and lasts
- condition does not improve or worsen after regular use of this product as directed

Keep out of reach of children

If swallowed, get medical help or contact a Poison Control Center (1-800-222-1222) right away.

Directions

1. Wet soap to generate foam to cover desired part of face or body

2. Massage foam well into the skin rubbing gently.

3. Rinse after 3-5 min.

4. Pat dry with soft cloth, leaving bit of moisture.

5. Repeat 2-3 times daily as needed.

Inactive ingredients

Sekken Soji, Alkoxy Glycerol, Grape Seed Oil, Tocophenol, Charcoal, Pure Water